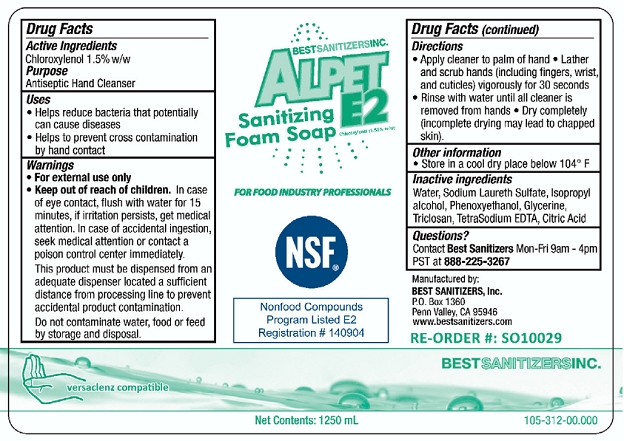 DRUG LABEL: Alpet E2 Sanitizing Foam
NDC: 59900-208 | Form: SOAP
Manufacturer: Best Sanitizers, Inc.
Category: otc | Type: HUMAN OTC DRUG LABEL
Date: 20241205

ACTIVE INGREDIENTS: CHLOROXYLENOL 15 g/1000 mL
INACTIVE INGREDIENTS: SODIUM LAURETH SULFATE; WATER; ISOPROPYL ALCOHOL; PHENOXYETHANOL; GLYCERIN; TRICLOSAN; EDETATE SODIUM; CITRIC ACID MONOHYDRATE

Alpet E2 Sanitizing Foam Soap 59900-208

Active Ingredient

Chloroxylenol 1.5% w/w

Purpose

Antiseptic Hand Cleanser

Uses

- Helps reduce bacteria that potentially can cause diseases
- Helps to prevent cross contamination by hand contact

Warnings

- For external use only

Keep out of reach of children.
In case of eye contact, flush with water for 15 minutes, if irritation persists, get medical attention.
In case of accidental ingestion, seek medical attention or contact a poison control center immediately.
This product must be dispensed from an adequate dispenser located a sufficient distance from processing line to prevent accidental product contamination.
Do not contaminate water, food or feed by storage and disposal.

Directions

- Apply cleaner to palm of hand
- Lather and scrub hands (including fingers, wrist, and cuticles) vigorously for 30 seconds
- Rinse with water until all cleaner is removed from hands
- Dry completely (incomplete drying may lead to happed skin)

Other information

- Store in a cool dry place below 104° F

Inactive ingredients

Water, Sodium Laureth Sulfate, Isopropyl alcohol, Phenoxyethanol, Glycerine, Triclosan, TetraSodium EDTA, Citric Acid

Questions?

Contact Best SanitizersMon-Fri 9am - 4p PST at 888-225-3267

PACKAGE LABEL

NDC: 59900-208-01

NDC: 59900-208-02

NDC: 59900-208-03

NDC: 59900-208-04

NDC: 59900-208-05

NDC: 59900-208-06

NDC: 59900-208-07

NDC: 59900-208-08

NDC: 59900-208-09

Alpet E2 Sanitizing Foam Soap

For Food Industry Professionals